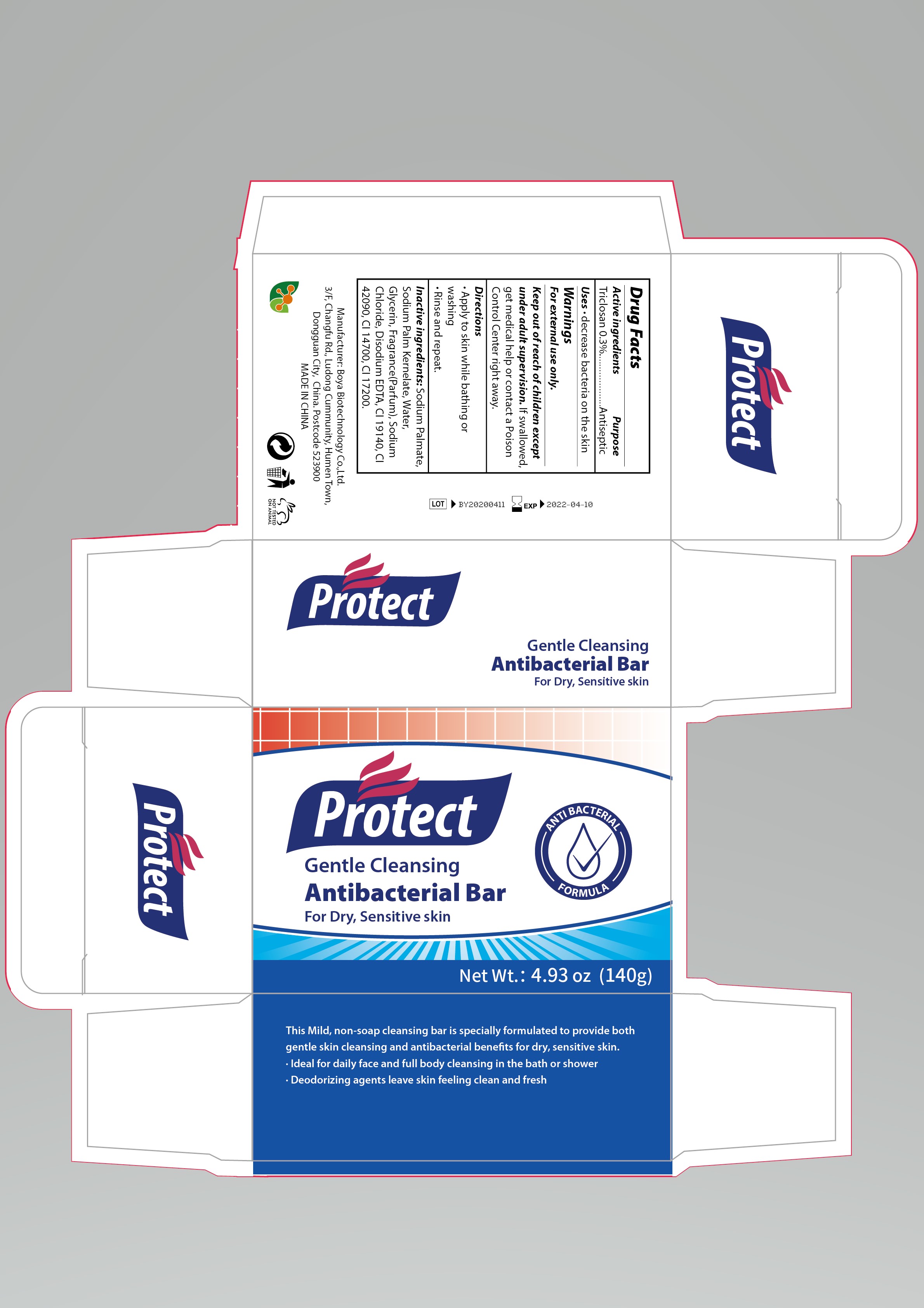 DRUG LABEL: Protect Antibacterial Bar
NDC: 73885-002 | Form: SOAP
Manufacturer: Boya Biotechnology Company Limited
Category: otc | Type: HUMAN OTC DRUG LABEL
Date: 20200426

ACTIVE INGREDIENTS: TRICLOSAN 0.3 g/100 g
INACTIVE INGREDIENTS: SODIUM PALMATE; SODIUM PALM KERNELATE; WATER; GLYCERIN; SODIUM CHLORIDE; DISODIUM HEDTA

Active Ingredient(s)

Triclosan 0.3%

Purpose

Antiseptic

Use

Decrease bacteria on the skin

Warnings

For external use only.

Stop use and ask a doctor if redness or irritation develops and persist for more than 72 hours

Keep out of reach of children except under adult supervision. If swallowed, get medical help or contact a Poison Control Center right away.

Directions

Apply to skin while bathing or washing

Rinse and repeat

Inactive ingredients

Sodium Palmate, Sodium Palm Kernelate, Water, Glycerin, Fragrance, Sodium Chloride, Disodium EDTA, CI 19140, CI 42090, CI 14700, CI 17200